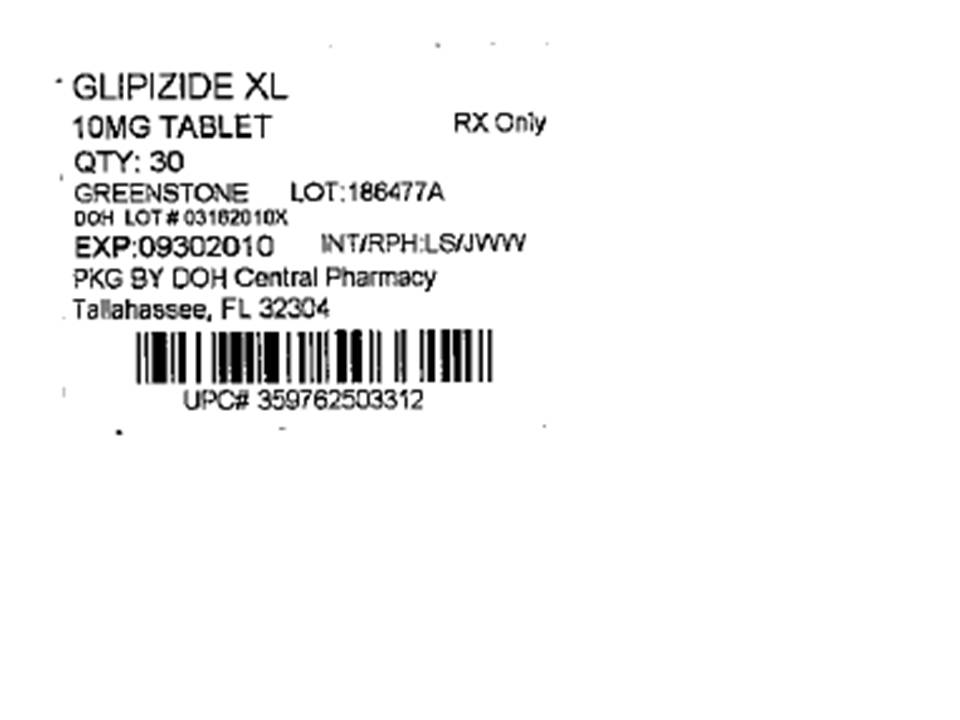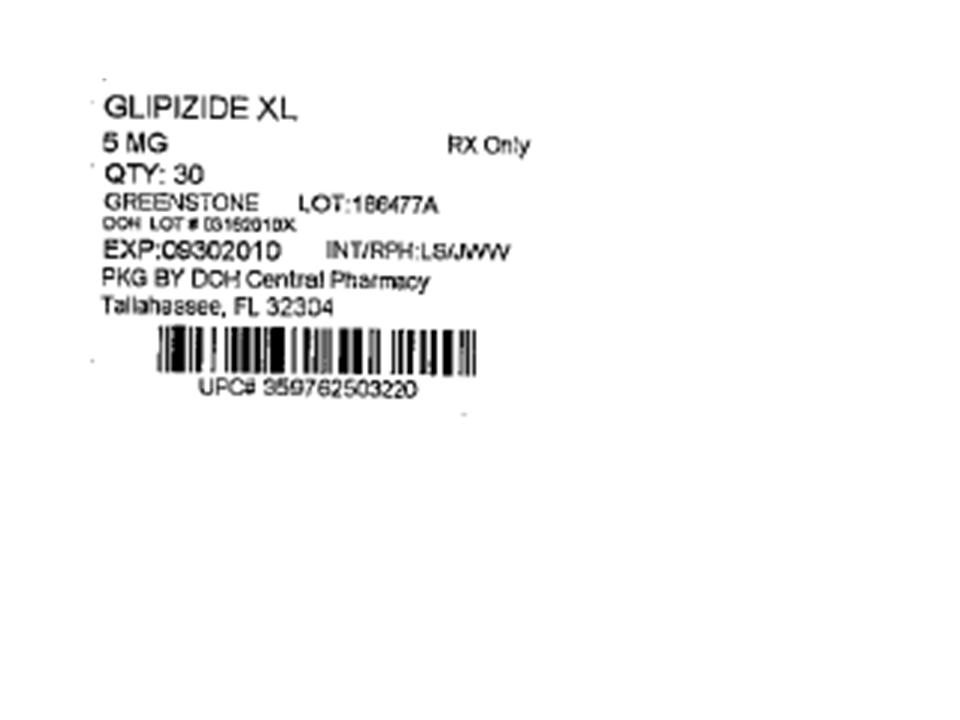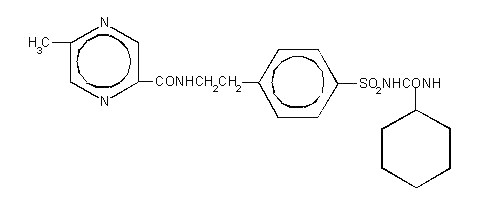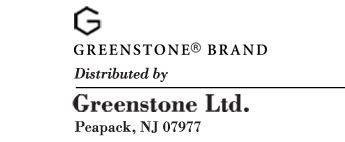 DRUG LABEL: Glipizide XL
NDC: 53808-0409 | Form: TABLET, EXTENDED RELEASE
Manufacturer: State of Florida DOH Central Pharmacy
Category: prescription | Type: HUMAN PRESCRIPTION DRUG LABEL
Date: 20100602

ACTIVE INGREDIENTS: GLIPIZIDE 5 mg/1 1
INACTIVE INGREDIENTS: POLYETHYLENE GLYCOL; HYPROMELLOSE; MAGNESIUM STEARATE; SODIUM CHLORIDE; FERRIC OXIDE RED; CELLULOSE ACETATE

Glipizide XL
(glipizide)
extended-release tablets
For Oral Use

DESCRIPTION

Glipizide is an oral blood-glucose-lowering drug of the sulfonylurea class.

The Chemical Abstracts name of glipizide is 1-cyclohexyl-3-[[p-[2-(5-methylpyrazinecarboxamido)ethyl] phenyl]sulfonyl]urea. The molecular formula is C21H27N5O4S; the molecular weight is 445.55; the structural formula is shown below:

Glipizide is a whitish, odorless powder with a pKa of 5.9. It is insoluble in water and alcohols, but soluble in 0.1 N NaOH; it is freely soluble in dimethylformamide. Glipizide XL is the Greenstone brand name for glipizide GITS.Glipizide GITS (Gastrointestinal Therapeutic System) is formulated as a once-a-day controlled release tablet for oral use and is designed to deliver 2.5, 5, or 10 mg of glipizide.

Inert ingredients in the 2.5 mg, 5 mg and 10 mg formulations are: polyethylene oxide, hypromellose, magnesium stearate, sodium chloride, red ferric oxide, cellulose acetate, polyethylene glycol, Opadry® blue (OY-LS-20921)(2.5 mg tablets), Opadry® white (YS-2-7063)(5 mg and 10 mg tablet) and black ink (S-1-8106).

System Components and Performance

Glipizide XL extended-release tablet is similar in appearance to a conventional tablet. It consists, however, of an osmotically active drug core surrounded by a semipermeable membrane. The core itself is divided into two layers: an "active" layer containing the drug, and a "push" layer containing pharmacologically inert (but osmotically active) components. The membrane surrounding the tablet is permeable to water but not to drug or osmotic excipients. As water from the gastrointestinal tract enters the tablet, pressure increases in the osmotic layer and "pushes" against the drug layer, resulting in the release of drug through a small, laser-drilled orifice in the membrane on the drug side of the tablet.

The Glipizide XL extended-release tablet is designed to provide a controlled rate of delivery of glipizide into the gastrointestinal lumen which is independent of pH or gastrointestinal motility. The function of the Glipizide XL extended-release tablet depends upon the existence of an osmotic gradient between the contents of the bi-layer core and fluid in the GI tract. Drug delivery is essentially constant as long as the osmotic gradient remains constant, and then gradually falls to zero. The biologically inert components of the tablet remain intact during GI transit and are eliminated in the feces as an insoluble shell.

CLINICAL PHARMACOLOGY

Mechanism of Action

Glipizide appears to lower blood glucose acutely by stimulating the release of insulin from the pancreas, an effect dependent upon functioning beta cells in the pancreatic islets. Extrapancreatic effects also may play a part in the mechanism of action of oral sulfonylurea hypoglycemic drugs. Two extrapancreatic effects shown to be important in the action of glipizide are an increase in insulin sensitivity and a decrease in hepatic glucose production. However, the mechanism by which glipizide lowers blood glucose during long-term administration has not been clearly established. Stimulation of insulin secretion by glipizide in response to a meal is of major importance. The insulinotropic response to a meal is enhanced with Glipizide XL administration in diabetic patients. The postprandial insulin and C-peptide responses continue to be enhanced after at least 6 months of treatment. In 2 randomized, double-blind, dose-response studies comprising a total of 347 patients, there was no significant increase in fasting insulin in all Glipizide XL-treated patients combined compared to placebo, although minor elevations were observed at some doses. There was no increase in fasting insulin over the long term.

Some patients fail to respond initially, or gradually lose their responsiveness to sulfonylurea drugs, including glipizide. Alternatively, glipizide may be effective in some patients who have not responded or have ceased to respond to other sulfonylureas.

Effects on Blood Glucose

The effectiveness of Glipizide XL extended-release tablets in type 2 diabetes at doses from 5–60 mg once daily has been evaluated in 4 therapeutic clinical trials each with long-term open extensions involving a total of 598 patients. Once daily administration of 5, 10 and 20 mg produced statistically significant reductions from placebo in hemoglobin A1C, fasting plasma glucose and postprandial glucose in patients with mild to severe type 2 diabetes. In a pooled analysis of the patients treated with 5 mg and 20 mg, the relationship between dose and Glipizide XL's effect of reducing hemoglobin A1C was not established. However, in the case of fasting plasma glucose patients treated with 20 mg had a statistically significant reduction of fasting plasma glucose compared to the 5 mg-treated group.

The reductions in hemoglobin A1C and fasting plasma glucose were similar in younger and older patients. Efficacy of Glipizide XL was not affected by gender, race or weight (as assessed by body mass index). In long term extension trials, efficacy of Glipizide XL was maintained in 81% of patients for up to 12 months.

In an open, two-way crossover study 132 patients were randomly assigned to either Glipizide XL or glipizide tablets for 8 weeks and then crossed over to the other drug for an additional 8 weeks. Glipizide XL administration resulted in significantly lower fasting plasma glucose levels and equivalent hemoglobin A1C levels, as compared to glipizide.

In 12 week, well-controlled studies there was a maximal average net reduction in hemoglobin A1c of 1.7% in absolute units between placebo-treated and GLIPIZIDE XL-treated patients.

Other Effects

It has been shown that Glipizide XL therapy is effective in controlling blood glucose without deleterious changes in the plasma lipoprotein profiles of patients treated for type 2 diabetes.

In a placebo-controlled, crossover study in normal volunteers, glipizide had no antidiuretic activity, and, in fact, led to a slight increase in free water clearance.

Pharmacokinetics and Metabolism

Glipizide is rapidly and completely absorbed following oral administration in an immediate release dosage form. The absolute bioavailability of glipizide was 100% after single oral doses in patients with type 2 diabetes. Beginning 2 to 3 hours after administration of Glipizide XL extended-release tablets, plasma drug concentrations gradually rise reaching maximum concentrations within 6 to 12 hours after dosing. With subsequent once daily dosing of Glipizide XL extended-release tablets, effective plasma glipizide concentrations are maintained throughout the 24 hour dosing interval with less peak to trough fluctuation than that observed with twice daily dosing of immediate release glipizide. The mean relative bioavailability of glipizide in 21 males with type 2 diabetes after administration of 20 mg Glipizide XL extended-release tablets, compared to immediate release glipizide (10 mg given twice daily), was 90% at steady-state. Steady-state plasma concentrations were achieved by at least the fifth day of dosing with Glipizide XL extended-release tablets in 21 males with type 2 diabetes and patients younger than 65 years. Approximately 1 to 2 days longer were required to reach steady-state in 24 elderly (≥65 years) males and females with type 2 diabetes. No accumulation of drug was observed in patients with type 2 diabetes during chronic dosing with Glipizide XL extended-release tablets. Administration of Glipizide XL with food has no effect on the 2 to 3 hour lag time in drug absorption. In a single dose, food effect study in 21 healthy male subjects, the administration of Glipizide XL immediately before a high fat breakfast resulted in a 40% increase in the glipizide mean Cmax value, which was significant, but the effect on the AUC was not significant. There was no change in glucose response between the fed and fasting state. Markedly reduced GI retention times of the Glipizide XL tablets over prolonged periods (e.g., short bowel syndrome) may influence the pharmacokinetic profile of the drug and potentially result in lower plasma concentrations. In a multiple dose study in 26 males with type 2 diabetes, the pharmacokinetics of glipizide were linear over the dose range of 5 to 60 mg of Glipizide XL in that the plasma drug concentrations increased proportionately with dose. In a single dose study in 24 healthy subjects, four 5 mg, two 10 mg, and one 20 mg Glipizide XL extended-release tablets were bioequivalent. In a separate single dose study in 36 healthy subjects, four 2.5-mg Glipizide XL extended-release tablets were bioequivalent to one 10-mg Glipizide XL extended-release tablet.

Glipizide is eliminated primarily by hepatic biotransformation: less than 10% of a dose is excreted as unchanged drug in urine and feces; approximately 90% of a dose is excreted as biotransformation products in urine (80%) and feces (10%). The major metabolites of glipizide are products of aromatic hydroxylation and have no hypoglycemic activity. A minor metabolite which accounts for less than 2% of a dose, an acetylamino-ethyl benzene derivative, is reported to have 1/10 to 1/3 as much hypoglycemic activity as the parent compound. The mean total body clearance of glipizide was approximately 3 liters per hour after single intravenous doses in patients with type 2 diabetes. The mean apparent volume of distribution was approximately 10 liters. Glipizide is 98–99% bound to serum proteins, primarily to albumin. The mean terminal elimination half-life of glipizide ranged from 2 to 5 hours after single or multiple doses in patients with type 2 diabetes. There were no significant differences in the pharmacokinetics of glipizide after single dose administration to older diabetic subjects compared to younger healthy subjects. There is only limited information regarding the effects of renal impairment on the disposition of glipizide, and no information regarding the effects of hepatic disease. However, since glipizide is highly protein bound and hepatic biotransformation is the predominant route of elimination, the pharmacokinetics and/or pharmacodynamics of glipizide may be altered in patients with renal or hepatic impairment.

In mice no glipizide or metabolites were detectable autoradiographically in the brain or spinal cord of males or females, nor in the fetuses of pregnant females. In another study, however, very small amounts of radioactivity were detected in the fetuses of rats given labelled drug.

INDICATIONS AND USAGE

Glipizide XL is indicated as an adjunct to diet and exercise to improve glycemic control in adults with type 2 diabetes mellitus.

CONTRAINDICATIONS

Glipizide is contraindicated in patients with:

1. Known hypersensitivity to glipizide or any excipients in the GITS tablets.
2. Type 1 diabetes mellitus, diabetic ketoacidosis, with or without coma. This condition should be treated with insulin.

WARNINGS

SPECIAL WARNING ON INCREASED RISK OF CARDIOVASCULAR MORTALITY

The administration of oral hypoglycemic drugs has been reported to be associated with increased cardiovascular mortality as compared to treatment with diet alone or diet plus insulin. This warning is based on the study conducted by the University Group Diabetes Program (UGDP), a long-term prospective clinical trial designed to evaluate the effectiveness of glucose-lowering drugs in preventing or delaying vascular complications in patients with type 2 diabetes. The study involved 823 patients who were randomly assigned to one of four treatment groups (Diabetes, 19, SUPP. 2: 747–830, 1970).

UGDP reported that patients treated for 5 to 8 years with diet plus a fixed dose of tolbutamide (1.5 grams per day) had a rate of cardiovascular mortality approximately 2½ times that of patients treated with diet alone. A significant increase in total mortality was not observed, but the use of tolbutamide was discontinued based on the increase in cardiovascular mortality, thus limiting the opportunity for the study to show an increase in overall mortality. Despite controversy regarding the interpretation of these results, the findings of the UGDP study provide an adequate basis for this warning. The patient should be informed of the potential risks and advantages of glipizide and of alternative modes of therapy.

Although only one drug in the sulfonylurea class (tolbutamide) was included in this study, it is prudent from a safety standpoint to consider that this warning may also apply to other oral hypoglycemic drugs in this class, in view of their close similarities in mode of action and chemical structure.

As with any other non-deformable material, caution should be used when administering Glipizide XL extended-release tablets in patients with preexisting severe gastrointestinal narrowing (pathologic or iatrogenic). There have been rare reports of obstructive symptoms in patients with known strictures in association with the ingestion of another drug in this non-deformable sustained release formulation.

PRECAUTIONS

Macrovascular Outcomes

There have been no clinical studies establishing conclusive evidence of macrovascular risk reduction with GLIPIZIDE XL or any other anti-diabetic drug.

Renal and Hepatic Disease

The pharmacokinetics and/or pharmacodynamics of glipizide may be affected in patients with impaired renal or hepatic function. If hypoglycemia should occur in such patients, it may be prolonged and appropriate management should be instituted.

GI Disease

Markedly reduced GI retention times of the Glipizide XL extended-release tablets may influence the pharmacokinetic profile and hence the clinical efficacy of the drug.

Hypoglycemia

All sulfonylurea drugs are capable of producing severe hypoglycemia. Proper patient selection, dosage, and instructions are important to avoid hypoglycemic episodes. Renal or hepatic insufficiency may affect the disposition of glipizide and the latter may also diminish gluconeogenic capacity, both of which increase the risk of serious hypoglycemic reactions. Elderly, debilitated or malnourished patients, and those with adrenal or pituitary insufficiency are particularly susceptible to the hypoglycemic action of glucose-lowering drugs. Hypoglycemia may be difficult to recognize in the elderly, and in people who are taking beta-adrenergic blocking drugs. Hypoglycemia is more likely to occur when caloric intake is deficient, after severe or prolonged exercise, when alcohol is ingested, or when more than one glucose-lowering drug is used. Therapy with a combination of glucose-lowering agents may increase the potential for hypoglycemia.

Loss of Control of Blood Glucose

When a patient stabilized on any diabetic regimen is exposed to stress such as fever, trauma, infection, or surgery, a loss of control may occur. At such times, it may be necessary to discontinue glipizide and administer insulin.

The effectiveness of any oral hypoglycemic drug, including glipizide, in lowering blood glucose to a desired level decreases in many patients over a period of time, which may be due to progression of the severity of the diabetes or to diminished responsiveness to the drug. This phenomenon is known as secondary failure, to distinguish it from primary failure in which the drug is ineffective in an individual patient when first given. Adequate adjustment of dose and adherence to diet should be assessed before classifying a patient as a secondary failure.

Hemolytic Anemia

Treatment of patients with glucose 6-phosphate dehydrogenase (G6PD) deficiency with sulfonylurea agents can lead to hemolytic anemia. Because GLIPIZIDE XL belongs to the class of sulfonylurea agents, caution should be used in patients with G6PD deficiency and a non-sulfonylurea alternative should be considered. In post marketing reports, hemolytic anemia has also been reported in patients who did not have known G6PD deficiency.

Laboratory Tests

Blood and urine glucose should be monitored periodically. Measurement of hemoglobin A1C may be useful.

Information for Patients

Patients should be informed that Glipizide XL extended-release tablets should be swallowed whole. Patients should not chew, divide or crush tablets. Patients should not be concerned if they occasionally notice in their stool something that looks like a tablet. In the Glipizide XL extended-release tablet, the medication is contained within a nonabsorbable shell that has been specially designed to slowly release the drug so the body can absorb it. When this process is completed, the empty tablet is eliminated from the body.

Patients should be informed of the potential risks and advantages of Glipizide XL and of alternative modes of therapy. They should also be informed about the importance of adhering to dietary instructions, of a regular exercise program, and of regular testing of urine and/or blood glucose.

The risks of hypoglycemia, its symptoms and treatment, and conditions that predispose to its development should be explained to patients and responsible family members. Primary and secondary failure also should be explained.

Physician Counseling Information for Patients

In initiating treatment for type 2 diabetes, diet should be emphasized as the primary form of treatment. Caloric restriction and weight loss are essential in the obese diabetic patient. Proper dietary management alone may be effective in controlling the blood glucose and symptoms of hyperglycemia. The importance of regular physical activity should also be stressed, and cardiovascular risk factors should be identified and corrective measures taken where possible. Use of GLIPIZIDE XL or other antidiabetic medications must be viewed by both the physician and patient as a treatment in addition to diet and not as a substitution or as a convenient mechanism for avoiding dietary restraint. Furthermore, loss of blood glucose control on diet alone may be transient, thus requiring only short-term administration of GLIPIZIDE XL or other antidiabetic medications. Maintenance or discontinuation of GLIPIZIDE XL or other antidiabetic medications should be based on clinical judgment using regular clinical and laboratory evaluations.

Drug Interactions

The hypoglycemic action of sulfonylureas may be potentiated by certain drugs including nonsteroidal anti-inflammatory agents and other drugs that are highly protein bound, salicylates, sulfonamides, chloramphenicol, probenecid, coumarins, monoamine oxidase inhibitors, and beta-adrenergic blocking agents. When such drugs are administered to a patient receiving glipizide, the patient should be observed closely for hypoglycemia. When such drugs are withdrawn from a patient receiving glipizide, the patient should be observed closely for loss of control. In vitro binding studies with human serum proteins indicate that glipizide binds differently than tolbutamide and does not interact with salicylate or dicumarol. However, caution must be exercised in extrapolating these findings to the clinical situation and in the use of glipizide with these drugs.

Certain drugs tend to produce hyperglycemia and may lead to loss of control. These drugs include the thiazides and other diuretics, corticosteroids, phenothiazines, thyroid products, estrogens, oral contraceptives, phenytoin, nicotinic acid, sympathomimetics, calcium channel blocking drugs, and isoniazid. When such drugs are administered to a patient receiving glipizide, the patient should be closely observed for loss of control. When such drugs are withdrawn from a patient receiving glipizide, the patient should be observed closely for hypoglycemia.

A potential interaction between oral miconazole and oral hypoglycemic agents leading to severe hypoglycemia has been reported. Whether this interaction also occurs with the intravenous, topical, or vaginal preparations of miconazole is not known. The effect of concomitant administration of Diflucan® (fluconazole) and glipizide tablets has been demonstrated in a placebo-controlled crossover study in normal volunteers. All subjects received glipizide tablets alone and following treatment with 100 mg of Diflucan® as a single daily oral dose for 7 days. The mean percentage increase in the glipizide tablets AUC after fluconazole administration was 56.9% (range: 35 to 81%).

Carcinogenesis, Mutagenesis, Impairment of Fertility

A twenty month study in rats and an eighteen month study in mice at doses up to 75 times the maximum human dose revealed no evidence of drug-related carcinogenicity. Bacterial and in vivo mutagenicity tests were uniformly negative. Studies in rats of both sexes at doses up to 75 times the human dose showed no effects on fertility.

Pregnancy Category C

Glipizide was found to be mildly fetotoxic in rat reproductive studies at all dose levels (5–50 mg/kg). This fetotoxicity has been similarly noted with other sulfonylureas, such as tolbutamide and tolazamide. The effect is perinatal and believed to be directly related to the pharmacologic (hypoglycemic) action of glipizide. In studies in rats and rabbits no teratogenic effects were found. There are no adequate and well controlled studies in pregnant women. Glipizide should be used during pregnancy only if the potential benefit justifies the potential risk to the fetus.

Because recent information suggests that abnormal blood-glucose levels during pregnancy are associated with a higher incidence of congenital abnormalities, many experts recommend that insulin be used during pregnancy to maintain blood-glucose levels as close to normal as possible.

Nonteratogenic Effects

Prolonged severe hypoglycemia (4 to 10 days) has been reported in neonates born to mothers who were receiving a sulfonylurea drug at the time of delivery. This has been reported more frequently with the use of agents with prolonged half-lives. If glipizide is used during pregnancy, it should be discontinued at least one month before the expected delivery date.

Nursing Mothers

Although it is not known whether glipizide is excreted in human milk, some sulfonylurea drugs are known to be excreted in human milk. Because the potential for hypoglycemia in nursing infants may exist, a decision should be made whether to discontinue nursing or to discontinue the drug, taking into account the importance of the drug to the mother. If the drug is discontinued and if diet alone is inadequate for controlling blood glucose, insulin therapy should be considered.

Pediatric Use

Safety and effectiveness in children have not been established.

Geriatric Use

Of the total number of patients in clinical studies of Glipizide XL, 33 percent were 65 and over. Approximately 1–2 days longer were required to reach steady-state in the elderly. (See CLINICAL PHARMACOLOGY and DOSAGE AND ADMINISTRATION.) There were no overall differences in effectiveness or safety between younger and older patients, but greater sensitivity of some individuals cannot be ruled out. As such, it should be noted that elderly, debilitated or malnourished patients, and those with adrenal or pituitary insufficiency, are particularly susceptible to the hypoglycemic action of glucose-lowering drugs. Hypoglycemia may be difficult to recognize in the elderly. In addition, in elderly, debilitated or malnourished patients, and patients with impaired renal or hepatic function, the initial and maintenance dosing should be conservative to avoid hypoglycemic reactions.

ADVERSE REACTIONS

In U.S. controlled studies the frequency of serious adverse experiences reported was very low and causal relationship has not been established.

The 580 patients from 31 to 87 years of age who received Glipizide XL extended-release tablets in doses from 5 mg to 60 mg in both controlled and open trials were included in the evaluation of adverse experiences. All adverse experiences reported were tabulated independently of their possible causal relation to medication.

Hypoglycemia

See PRECAUTIONS and OVERDOSAGE sections.

Only 3.4% of patients receiving Glipizide XL extended-release tablets had hypoglycemia documented by a blood-glucose measurement <60 mg/dL and/or symptoms believed to be associated with hypoglycemia. In a comparative efficacy study of Glipizide XL and glipizide tablets, hypoglycemia occurred rarely with an incidence of less than 1% with both drugs.

In double-blind, placebo-controlled studies the adverse experiences reported with an incidence of 3% or more in Glipizide XL-treated patients include:

 | Glipizide XL (%) | Placebo (%)
 | (N=278) | (N=69)
Adverse Effect
Asthenia | 10.1 | 13.0
Headache | 8.6 | 8.7
Dizziness | 6.8 | 5.8
Nervousness | 3.6 | 2.9
Tremor | 3.6 | 0.0
Diarrhea | 5.4 | 0.0
Flatulence | 3.2 | 1.4

The following adverse experiences occurred with an incidence of less than 3% in Glipizide XL-treated patients:

Body as a whole–pain
Nervous system–insomnia, paresthesia, anxiety, depression and hypesthesia
Gastrointestinal–nausea, dyspepsia, constipation and vomiting
Metabolic–hypoglycemia
Musculoskeletal–arthralgia, leg cramps and myalgia
Cardiovascular–syncope
Skin–sweating and pruritus
Respiratory–rhinitis
Special senses–blurred vision
Urogenital–polyuria

Other adverse experiences occurred with an incidence of less than 1% in Glipizide XL-treated patients:

Body as a whole–chills
Nervous system–hypertonia, confusion, vertigo, somnolence, gait abnormality and decreased libido
Gastrointestinal–anorexia and trace blood in stool
Metabolic–thirst and edema
Cardiovascular–arrhythmia, migraine, flushing and hypertension
Skin–rash and urticaria
Respiratory–pharyngitis and dyspnea
Special senses–pain in the eye, conjunctivitis and retinal hemorrhage
Urogenital–dysuria

Although these adverse experiences occurred in patients treated with Glipizide XL, a causal relationship to the medication has not been established in all cases.

There have been rare reports of gastrointestinal irritation and gastrointestinal bleeding with use of another drug in this non-deformable sustained release formulation, although causal relationship to the drug is uncertain.

In post-marketing experience of Glipizide XL, the additional adverse reaction of abdominal pain has been reported.

The following are adverse experiences reported with immediate release glipizide and other sulfonylureas, but have not been observed with Glipizide XL:

Hematologic

Leukopenia, agranulocytosis, thrombocytopenia, hemolytic anemia (see PRECAUTIONS), aplastic anemia, and pancytopenia have been reported with sulfonylureas.

Metabolic

Hepatic porphyria and disulfiram-like reactions have been reported with sulfonylureas. In the mouse, glipizide pretreatment did not cause an accumulation of acetaldehyde after ethanol administration. Clinical experience to date has shown that glipizide has an extremely low incidence of disulfiram-like alcohol reactions.

Endocrine Reactions

Cases of hyponatremia and the syndrome of inappropriate antidiuretic hormone (SIADH) secretion have been reported with glipizide and other sulfonylureas.

Laboratory Tests

The pattern of laboratory test abnormalities observed with glipizide was similar to that for other sulfonylureas. Occasional mild to moderate elevations of SGOT, LDH, alkaline phosphatase, BUN and creatinine were noted. One case of jaundice was reported. The relationship of these abnormalities to glipizide is uncertain, and they have rarely been associated with clinical symptoms.

OVERDOSAGE

There is no well-documented experience with Glipizide XL overdosage in humans. There have been no known suicide attempts associated with purposeful overdosing with Glipizide XL. In nonclinical studies the acute oral toxicity of glipizide was extremely low in all species tested (LD50 greater than 4 g/kg). Overdosage of sulfonylureas including glipizide can produce hypoglycemia. Mild hypoglycemic symptoms without loss of consciousness or neurologic findings should be treated aggressively with oral glucose and adjustments in drug dosage and/or meal patterns. Close monitoring should continue until the physician is assured that the patient is out of danger. Severe hypoglycemic reactions with coma, seizure, or other neurological impairment occur infrequently, but constitute medical emergencies requiring immediate hospitalization. If hypoglycemic coma is diagnosed or suspected, the patient should be given rapid intravenous injection of concentrated (50%) glucose solution. This should be followed by a continuous infusion of a more dilute (10%) glucose solution at a rate that will maintain the blood glucose at a level above 100 mg/dL. Patients should be closely monitored for a minimum of 24 to 48 hours since hypoglycemia may recur after apparent clinical recovery. Clearance of glipizide from plasma may be prolonged in persons with liver disease. Because of the extensive protein binding of glipizide, dialysis is unlikely to be of benefit.

DOSAGE AND ADMINISTRATION

There is no fixed dosage regimen for the management of diabetes mellitus with Glipizide XL extended-release tablet or any other hypoglycemic agent. Glycemic control should be monitored with hemoglobin A1C and/or blood-glucose levels to determine the minimum effective dose for the patient; to detect primary failure, i.e., inadequate lowering of blood glucose at the maximum recommended dose of medication; and to detect secondary failure, i.e., loss of an adequate blood-glucose-lowering response after an initial period of effectiveness. Home blood-glucose monitoring may also provide useful information to the patient and physician. Short-term administration of Glipizide XL extended-release tablet may be sufficient during periods of transient loss of control in patients usually controlled on diet.

In general, Glipizide XL should be given with breakfast.

Recommended Dosing

The usual starting dose of Glipizide XL as initial therapy is 5 mg per day, given with breakfast. Those patients who may be more sensitive to hypoglycemic drugs may be started at a lower dose.

Dosage adjustment should be based on laboratory measures of glycemic control. While fasting blood-glucose levels generally reach steady-state following initiation or change in Glipizide XL dosage, a single fasting glucose determination may not accurately reflect the response to therapy. In most cases, hemoglobin A1C level measured at three month intervals is the preferred means of monitoring response to therapy.

Hemoglobin A1C should be measured as Glipizide XL therapy is initiated and repeated approximately three months later. If the result of this test suggests that glycemic control over the preceding three months was inadequate, the Glipizide XL dose may be increased. Subsequent dosage adjustments should be made on the basis of hemoglobin A1C levels measured at three month intervals. If no improvement is seen after three months of therapy with a higher dose, the previous dose should be resumed. Decisions which utilize fasting blood glucose to adjust Glipizide XL therapy should be based on at least two or more similar, consecutive values obtained seven days or more after the previous dose adjustment.

Most patients will be controlled with 5 mg to 10 mg taken once daily. However, some patients may require up to the maximum recommended daily dose of 20 mg. While the glycemic control of selected patients may improve with doses which exceed 10 mg, clinical studies conducted to date have not demonstrated an additional group average reduction of hemoglobin A1C beyond what was achieved with the 10 mg dose.

Based on the results of a randomized crossover study, patients receiving immediate release glipizide may be switched safely to Glipizide XL extended-release tablets once-a-day at the nearest equivalent total daily dose. Patients receiving immediate release glipizide tablets also may be titrated to the appropriate dose of Glipizide XL starting with 5 mg once daily. The decision to switch to the nearest equivalent dose or to titrate should be based on clinical judgment.

In elderly patients, debilitated or malnourished patients, and patients with impaired renal or hepatic function, the initial and maintenance dosing should be conservative to avoid hypoglycemic reactions (see PRECAUTIONS section).

Combination Use

When adding other blood-glucose-lowering agents to Glipizide XL for combination therapy, the agent should be initiated at the lowest recommended dose, and patients should be observed carefully for hypoglycemia. Refer to the product information supplied with the oral agent for additional information.

When adding Glipizide XL to other blood-glucose-lowering agents, Glipizide XL can be initiated at 5 mg. Those patients who may be more sensitive to hypoglycemic drugs may be started at a lower dose. Titration should be based on clinical judgment.

Patients Receiving Insulin

As with other sulfonylurea-class hypoglycemics, many patients with stable type 2 diabetes receiving insulin may be transferred safely to treatment with Glipizide XL extended-release tablets. When transferring patients from insulin to Glipizide XL, the following general guidelines should be considered:

For patients whose daily insulin requirement is 20 units or less, insulin may be discontinued and Glipizide XL therapy may begin at usual dosages. Several days should elapse between titration steps.

For patients whose daily insulin requirement is greater than 20 units, the insulin dose should be reduced by 50% and Glipizide XL therapy may begin at usual dosages. Subsequent reductions in insulin dosage should depend on individual patient response. Several days should elapse between titration steps.

During the insulin withdrawal period, the patient should test urine samples for sugar and ketone bodies at least three times daily. Patients should be instructed to contact the prescriber immediately if these tests are abnormal. In some cases, especially when the patient has been receiving greater than 40 units of insulin daily, it may be advisable to consider hospitalization during the transition period.

Patients Receiving Other Oral Hypoglycemic Agents

As with other sulfonylurea-class hypoglycemics, no transition period is necessary when transferring patients to Glipizide XL extended-release tablets. Patients should be observed carefully (1–2 weeks) for hypoglycemia when being transferred from longer half-life sulfonylureas (e.g., chlorpropamide) to Glipizide XL due to potential overlapping of drug effect.

HOW SUPPLIED

Glipizide XL (glipizide) extended-release tablets are supplied as 2.5 mg, 5 mg, and 10 mg round, biconvex tablets and imprinted with black ink.

They are supplied by State of Florida DOH Central Pharmacy as follows:

NDC | Strength | Quantity/Form | Color | Source Prod. Code
53808-0409-1 | 5 mg | 30 Tablets in a Blister Pack | WHITE | 59762-5032
53808-0408-1 | 10 mg | 30 Tablets in a Blister Pack | WHITE | 59762-5033

Recommended Storage

The tablets should be protected from moisture and humidity and stored at controlled room temperature, 59° to 86°F (15° to 30°C).

Rx only

PATIENT INFORMATION

GLIPIZIDE XL
(glipizide extended release tablets)

Read this information carefully before you start taking this medicine. Read the information you get with your medicine each time you refill your prescription. There may be new information. This information does not take the place of your healthcare provider's advice. Ask your healthcare provider or pharmacist if you do not understand some of this information or if you want to know more about this medicine.

What is GLIPIZIDE XL?

GLIPIZIDE XL is a medicine you take by mouth. It is used to treat type 2 diabetes (also called non-insulin-dependant diabetes mellitus). Your healthcare provider has prescribed GLIPIZIDE XL because your current treatment, including diet and exercise, has not been able to bring your blood sugar level under good control.

Your body makes insulin to keep the amount of sugar (glucose) in your blood at the right level. With type 2 diabetes:

- your body may not be making enough insulin
- your body may not be using the insulin that you have already made
- the level of sugar in your blood is too high

If your blood sugar level is not under control, it can lead to serious medical problems, such as kidney damage, nerve damage, blindness, problems with circulation (blood movement in your body), loss of feet, legs or other limbs, high blood pressure, heart attack, or stroke.

GLIPIZIDE XL works mainly by:

- helping the body release more of its own insulin
- helping the body respond better to its own insulin
- lowering the amount of sugar (glucose) made by the body

Even after you start taking GLIPIZIDE XL, you must continue to follow your program of diet and exercise.

Who Should Not Use GLIPIZIDE XL?

Do not use GLIPIZIDE XL if you:

- have a condition called diabetic ketoacidosis
- have ever had an allergic reaction to glipizide or any of the other ingredients in GLIPIZIDE XL. Ask your healthcare provider or pharmacist for a list of these ingredients.

Only your healthcare provider can decide if GLIPIZIDE XL is right for you. Before you start GLIPIZIDE XL, tell the healthcare provider if you:

- are taking or using any prescription medicines or non-prescription medicines, including natural or herbal remedies. Other medications can increase your chance of getting low blood sugar or high blood sugar. Be sure to tell your healthcare provider if you take the medicines miconazole or fluconazole, used to fight fungus infections.
- have ever had a condition called diabetic ketoacidosis
- have kidney or liver problems
- have had blockage or narrowing of your intestines due to illness or past surgery
- have chronic (continuing) diarrhea
- are pregnant or might be pregnant. Your healthcare provider may switch you to insulin injections some time during your pregnancy. You should not take GLIPIZIDE XL during the last month of pregnancy
- are breast-feeding. GLIPIZIDE XL may pass to the baby through your milk and cause harm.
- have glucose-6-phosphate dehydrogenase (G6PD) deficiency. This condition usually runs in families. People with G6PD deficiency who take Glucotrol XL may develop hemolytic anemia (fast breakdown of red blood cells).

How Should I Take GLIPIZIDE XL?

GLIPIZIDE XL tablets come in three different strengths (2.5 mg, 5 mg and 10 mg). Your healthcare provider will prescribe the dose that is right for you.

- Take GLIPIZIDE XL once a day with breakfast. The tablet is designed to release the medicine slowly over 24 hours. This is why you have to take it only once a day.
- Swallow the tablet whole. Never chew, crush or cut the tablet in half. This would damage the tablet and release too much medicine into your body at one time.
- After all of the medicine has been released, the empty tablet shell will pass out of the body normally in a bowel movement. Do not be concerned if you see the empty tablet shell in your stool (bowel movement).

It is important to take GLIPIZIDE XL every day to help keep your blood sugar level under good control. Your healthcare provider may adjust your dose depending on your blood glucose test results. If your blood sugar level is not under control, call your healthcare provider. Do not change your dose without your healthcare provider's approval.

In case of overdose, call the poison control center or your healthcare provider right away, or have someone drive you to the nearest emergency room.

You must continue your diet and exercise program while taking GLIPIZIDE XL. You must also have your blood and urine tested regularly to be sure GLIPIZIDE XL is working.

GLIPIZIDE XL may not work for everyone. If it does work, you may find that GLIPIZIDE XL is not working as well for you after you have used it for a while. Tell your healthcare provider if GLIPIZIDE XL is not working well.

What Should I Avoid While Taking GLIPIZIDE XL?

Some medicines can affect how well GLIPIZIDE XL works or may affect your blood sugar level. Check with your healthcare provider or pharmacist before you start or stop taking prescription or over-the-counter medicines, including natural/herbal remedies, while on GLIPIZIDE XL.

What are the Possible Side Effects of GLIPIZIDE XL?

Low blood sugar. GLIPIZIDE XL may lower your blood sugar to low levels that are dangerous (hypoglycemia). This can happen if you do not follow your diet, exercise too much, drink alcohol, are under stress, or get sick. This could also happen if your dose of GLIPIZIDE XL is higher than you need. Your healthcare provider may need to adjust it. Do not adjust the dose on your own.

Be sure you know how to recognize your body's signs that your blood sugar is too low. These signs include:

- a cold clammy feeling
- unusual sweating
- dizziness
- weakness
- trembling
- shakiness
- hunger
- fast heartbeat
- headache
- blurred vision
- slurred speech
- tingling in the lips or hands

If you notice any of these signs, eat or drink something with sugar in it right away, such as a regular (not diet) soft drink, orange juice, honey, sugar candy. You can also keep glucose tablets on hand that are available at your pharmacy. If you do not feel better shortly or your blood sugar level does not go up, call your healthcare provider. If you cannot reach your healthcare provider in an emergency, call 911 or have someone drive you to the nearest emergency room.

Other side effects. GLIPIZIDE XL may cause other side effects in some people. However, the incidence of serious side effects with GLIPIZIDE XL is very low. Other than the signs of low blood sugar listed above, possible side effects include:

- feeling jittery
- diarrhea
- gas

GLIPIZIDE XL may cause other less common side effects besides those listed here. For a list of all side effects that have been reported, ask your healthcare provider or pharmacist.

While it has never been reported with GLIPIZIDE XL, another similar type of diabetes medicine has been linked to a higher risk of heart attacks. If you have risk factors for heart disease and take GLIPIZIDE XL, be sure to see your healthcare provider for regular checkups.

How To Store GLIPIZIDE XL

Keep GLIPIZIDE XL and all medicines out of reach of children. Store GLIPIZIDE XL in a dry place, in its original container, and at room temperature (between 59°–86° F or 15°–30° C).

General Advice About Prescription Medicines

Medicines are sometimes prescribed for purposes other than those listed in a patient information leaflet. If you have any concerns about GLIPIZIDE XL, ask your healthcare provider. Your healthcare provider or pharmacist can give you information about GLIPIZIDE XL that was written for healthcare professionals. Do not use GLIPIZIDE XL for a condition for which it was not prescribed. Do not share GLIPIZIDE XL with other people. For more information about GLIPIZIDE XL, you can visit the Pfizer internet site at www.pfizer.com.

This Product was Repackaged By:

State of Florida DOH Central Pharmacy
104-2 Hamilton Park Drive
Tallahassee, FL 32304
United States

Label Image 5mg

NDC 53808-0409-1
30 Tablets

GREENSTONE® BRAND

Glipizide XL
(glipizide)
extended-release
tablets

5 mg

Rx only

Label Image 10mg

NDC 53808-0408-1
30 Tablets

GREENSTONE® BRAND

Glipizide XL
(glipizide)
extended-release
tablets

10 mg

Rx only